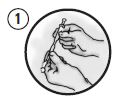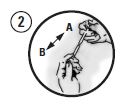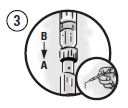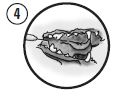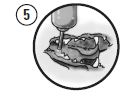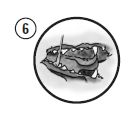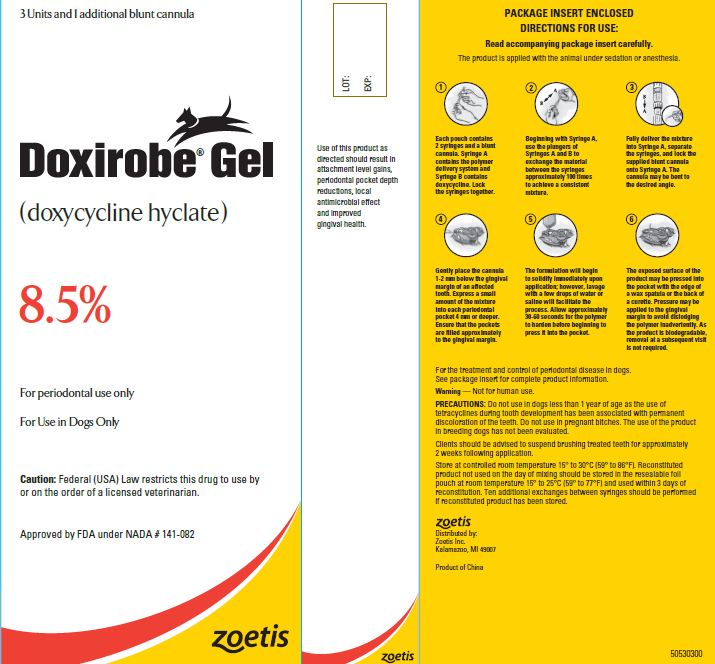 DRUG LABEL: Doxirobe
NDC: 54771-5193 | Form: GEL
Manufacturer: Zoetis Inc.
Category: animal | Type: PRESCRIPTION ANIMAL DRUG LABEL
Date: 20230707

ACTIVE INGREDIENTS: DOXYCYCLINE HYCLATE 42.5 mg/0.5 mL

Doxirobe® Gel

Doxirobe Gel

(doxycycline hyclate)

For Periodontal Use in Dogs Only

CAUTION

Federal law restricts this drug to use by or on the order of a licensed veterinarian.

DESCRIPTION

DOXIROBE Gel is provided in a 2-syringe system requiring mixing prior to use. Syringe A contains the polymer delivery system (N-methyl-2-pyrrolidone and poly (DL-lactide)) and Syringe B contains the active ingredient (doxycycline). Once mixed, the product is a flowable solution of doxycycline hyclate equivalent to 8.5% doxycycline activity. The formulation is applied subgingivally to the periodontal pocket(s) of affected teeth, and doxycycline is slowly released from the polymer providing a local antimicrobial effect. The product is non-irritating and biodegradable.

CLINICAL PHARMACOLOGY

Doxycycline is a semi-synthetic tetracycline derivative. Consistent with the tetracycline class of antibiotics, it has a wide range of antimicrobial activity against microorganisms. Upon contact with the aqueous environment (gingival crevicular fluid) the polymer will coagulate, resulting in the formation of a solid, pliable delivery system within the treated periodontal pocket(s). Doxycycline is released into the gingival crevicular fluid for a local effect on the microorganisms, particularly gram-negative anaerobic bacteria, involved in periodontal disease.

In a clinical trial, the highest plasma doxycycline concentration was observed at 6 hours after treatment administration (2-4 affected teeth in each of 6 dogs). Doxycycline was not detected in plasma samples taken at 24 hours after treatment administration or any time point thereafter. All detectable concentrations of doxycycline were well below levels associated with systemic activity or toxicity.

INDICATIONS AND USAGE

DOXIROBE Gel is indicated for the treatment and control of periodontal disease in dogs.
Periodontal pocket probing depths ≥ 4 mm are evidence of disease that may be responsive to treatment with DOXIROBE Gel. In clinical trials, use of the product resulted in attachment level gains, periodontal pocket depth reductions and improved gingival health. Noticeable improvements in these parameters should be evident within 2-4 weeks following treatment. The response in individual animals is dependent on the severity of the condition and rigor of adjunctive therapy. This product is not intended for use in oronasal fistulas, periapical abscesses, or severely compromised teeth.

PRECAUTIONS

Do not use in dogs less than 1 year of age as the use of tetracyclines during tooth development has been associated with permanent discoloration of the teeth. Do not use in pregnant bitches. The use of the product in breeding dogs has not been evaluated.

Clients should be advised to suspend brushing treated teeth for approximately 2 weeks following treatment.

DOSAGE AND ADMINISTRATION

Teeth should be cleaned and scaled prior to application of the product.

If required, root planing and debridement of affected sites should be performed. The product is applied with the animal under sedation or anesthesia. Use as many units as required to fill the periodontal pockets of affected teeth.

Picture 1

Each pouch contains 2 syringes and a blunt cannula. Syringe A contains the polymer delivery system and Syringe B contains doxycycline. Lock the syringes together.

Picture 2

Beginning with Syringe A, use the plungers of Syringes A and B to exchange the material between the syringes approximately 100 times to achieve a consistent mixture.

Picture 3

Fully deliver the mixture into Syringe A, separate the syringes, and lock the supplied blunt cannula onto Syringe A. The cannula may be bent to the desired angle.

Picture 4

Gently place the cannula 1-2 mm below the gingival margin of an affected tooth. Express a small amount of the mixture into each periodontal pocket 4 mm or deeper. Ensure that the pockets are filled approximately to the gingival margin.

Picture 5

The formulation will begin to solidify immediately upon application; however, lavage with a few drops of water or saline will facilitate the process. Allow approximately 30-60 seconds for the polymer to harden before beginning to press it into the pocket

Picture 6

The exposed surface of the product may be pressed into the pocket with the edge of a wax spatula or the back of a curette. Pressure may be applied to the gingival margin to avoid dislodging the polymer inadvertently. As the product is biodegradable, removal at a subsequent visit is not required.

Treatment and control of periodontal disease requires a comprehensive program of routine scaling and cleaning, home care and dental hygiene (e.g., brushing, rinses or the use of chewing devices) in addition to application of this product. Severe cases may require surgical intervention.
Reconstituted product not used on the day of mixing should be stored in the resealable foil pouch at room temperature (15-25°C or 59-77°F) and used within 3 days of reconstitution. Ten additional exchanges between syringes should be performed if reconstituted product has been stored.

STORAGE CONDITIONS

Store at controlled room temperature 15° to 30°C (59° to 86°F).

HOW SUPPLIED

Each unit of DOXIROBE Gel contains Syringe A (polymer delivery system) and Syringe B (doxycycline), which when mixed result in approximately 0.5 ml of doxycycline solution. Available as a 3-unit carton (containing 1 additional blunt cannula), NDC 0009-5193-01.

Approved by FDA under NADA # 141-082

To report suspected adverse events, for technical assistance or to obtain a copy of the SDS, contact Zoetis Inc. at 1-888-963-8471 or www.zoetis.com.

For additional information about adverse drug experience reporting for animal drugs, contact FDA at 1-888-FDA-VETS or online at www.fda.gov/reportanimalae.

zoetis

Distributed by:
Zoetis Inc.
Kalamazoo, MI 49007

Revised: April 2020

50530401